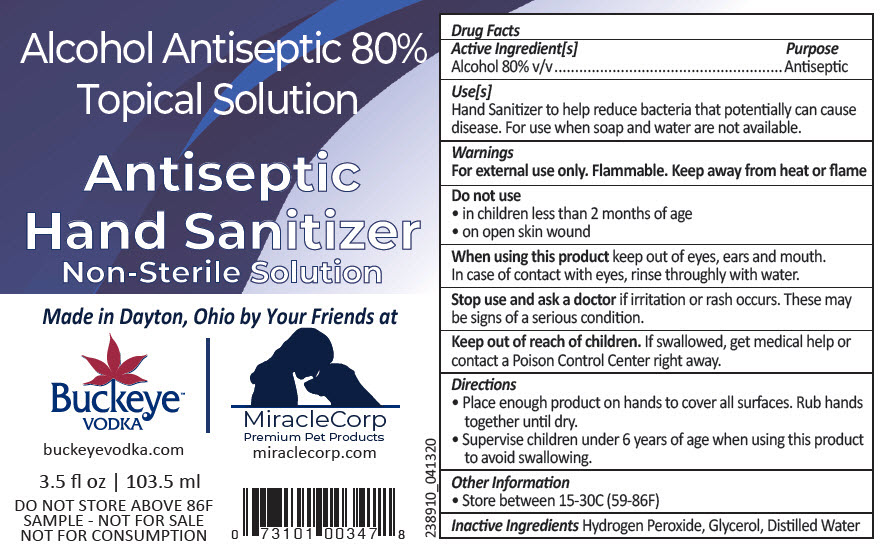 DRUG LABEL: Antiseptic Hand Sanitizer
NDC: 61429-005 | Form: SPRAY
Manufacturer: MiracleCorp Products
Category: otc | Type: HUMAN OTC DRUG LABEL
Date: 20200427

ACTIVE INGREDIENTS: Alcohol 80 mL/100 mL
INACTIVE INGREDIENTS: Hydrogen Peroxide; Glycerin; Water

Antiseptic Hand Sanitizer

Drug Facts

Active Ingredient[s]

Alcohol 80% v/v

Purpose

Antiseptic

Use[s]

Hand Sanitizer to help reduce bacteria that potentially can cause disease. For use when soap and water are not available.

Warnings

For external use only. Flammable. Keep away from heat or flame

Do not use

- in children less than 2 months of age
- on open skin wound

When using this product keep out of eyes, ears and mouth. In case of contact with eyes, rinse throughly with water.

Stop use and ask a doctor if irritation or rash occurs. These may be signs of a serious condition.

Keep out of reach of children. If swallowed, get medical help or contact a Poison Control Center right away.

Directions

- Place enough product on hands to cover all surfaces. Rub hands together until dry.
- Supervise children under 6 years of age when using this product to avoid swallowing.

Other Information

- Store between 15-30C (59-86F)

Inactive Ingredients

Hydrogen Peroxide, Glycerol, Distilled Water

PRINCIPAL DISPLAY PANEL - 103.5 ml Bottle Label

Alcohol Antiseptic 80%
Topical Solution

Antiseptic
Hand Sanitizer
Non-Sterile Solution

Made in Dayton, Ohio by Your Friends at

Buckeye™
VODKA

buckeyevodka.com

MiracleCorp
Premium Pet Products
miraclecorp.com

3.5 fl oz | 103.5 ml

DO NOT STORE ABOVE 86F
SAMPLE - NOT FOR SALE
NOT FOR CONSUMPTION

238910_041320